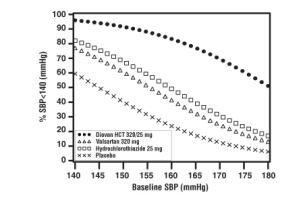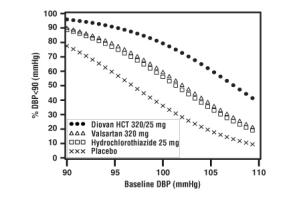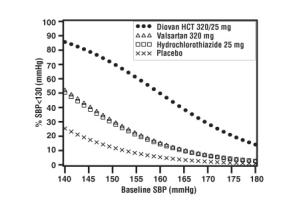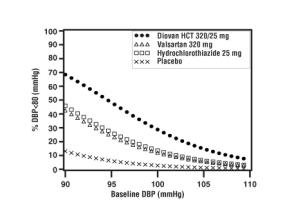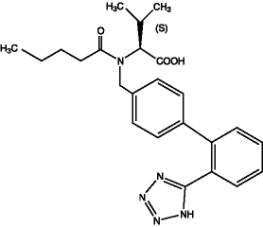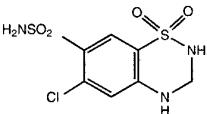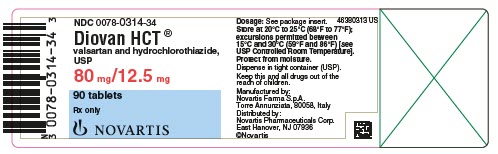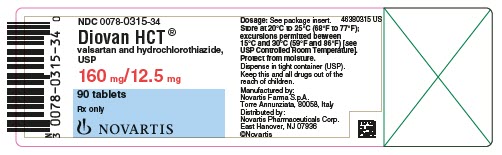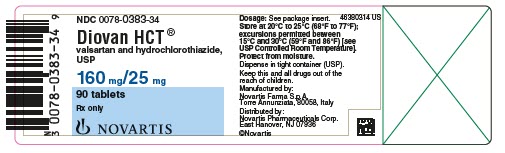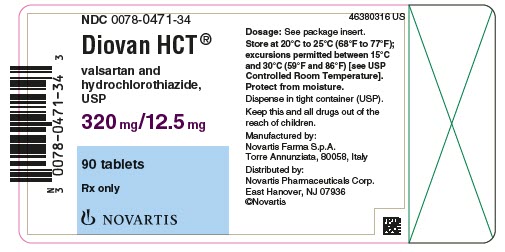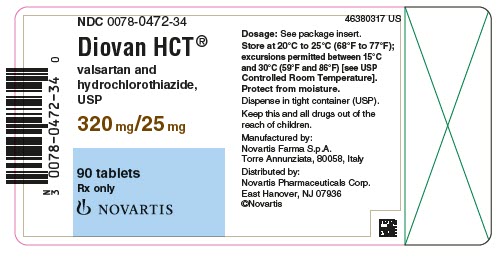 DRUG LABEL: Diovan HCT
NDC: 0078-0314 | Form: TABLET, FILM COATED
Manufacturer: Novartis Pharmaceuticals Corporation
Category: prescription | Type: HUMAN PRESCRIPTION DRUG LABEL
Date: 20260213

ACTIVE INGREDIENTS: VALSARTAN 80 mg/1 1; HYDROCHLOROTHIAZIDE 12.5 mg/1 1
INACTIVE INGREDIENTS: SILICON DIOXIDE; CROSPOVIDONE; HYPROMELLOSES; FERRIC OXIDE RED; MAGNESIUM STEARATE; CELLULOSE, MICROCRYSTALLINE; POLYETHYLENE GLYCOL; TALC; TITANIUM DIOXIDE

HIGHLIGHTS OF PRESCRIBING INFORMATION

These highlights do not include all the information needed to use DIOVAN HCT safely and effectively. See full prescribing information for DIOVAN HCT.
DIOVAN HCT® (valsartan and hydrochlorothiazide USP) tablets, for oral use
Initial U.S. Approval: 1998

WARNING: FETAL TOXICITY

See full prescribing information for complete boxed warning.

- When pregnancy is detected, discontinue Diovan HCT as soon as possible. (5.1)
- Drugs that act directly on the renin-angiotensin system can cause injury and death to the developing fetus. (5.1)

1 INDICATIONS AND USAGE

Diovan HCT is the combination tablet of valsartan (Diovan), an angiotensin II receptor blocker (ARB) and hydrochlorothiazide (HCTZ), a diuretic. Diovan HCT is indicated for the treatment of hypertension, to lower blood pressure:

- In patients not adequately controlled with monotherapy (1)
- As initial therapy in patients likely to need multiple drugs to achieve their blood pressure goals (1)

Lowering blood pressure reduces the risk of fatal and nonfatal cardiovascular events, primarily strokes and myocardial infarctions.

2 DOSAGE AND ADMINISTRATION

- Dose once daily. Titrate as needed to a maximum dose of 320/25mg. (2)
- May be used as add-on/switch therapy for patients not adequately controlled on any of the components (valsartan or HCTZ). (2)
- May be substituted for titrated components. (2.3)

3 DOSAGE FORMS AND STRENGTHS

Tablets (valsartan/HCTZ mg): 80/12.5, 160/12.5, 160/25, 320/12.5, 320/25 (3)

4 CONTRAINDICATIONS

Anuria; Hypersensitivity to any sulfonamide-derived drugs or any component;
Do not coadminister aliskiren with Diovan HCT in patients with diabetes. (4)

5 WARNINGS AND PRECAUTIONS

- Hypotension: Correct volume depletion prior to initiation (5.2)
- Observe for signs of fluid or electrolyte imbalance (5.9)
- Monitor renal function and potassium in susceptible patients (5.3, 5.7)
- Exacerbation or activation of systemic lupus erythematosus (5.5)
- Acute angle-closure glaucoma (5.8)

6 ADVERSE REACTIONS

The most common reasons for discontinuation of therapy with Diovan HCT were headache and dizziness. The only adverse experience that occurred in ≥ 2% of patients treated with Diovan HCT and at a higher incidence than placebo was nasopharyngitis (2.4% vs. 1.9%). (6.1)

To report SUSPECTED ADVERSE REACTIONS, contact Novartis Pharmaceuticals Corporation at 1-888-669-6682 or FDA at 1-800-FDA-1088 or www.fda.gov/medwatch.

7 DRUG INTERACTIONS

- Antidiabetic drugs: Dosage adjustment of antidiabetic may be required. (7)
- Cholestyramine and colestipol: Reduced absorption of thiazides. (12.3)
- Lithium: Increased risk of lithium toxicity. Monitor serum lithium concentrations during concurrent use. (7)
- Non-Steroidal Anti-Inflammatory Drugs (NSAIDs): May increase risk of renal impairment. Can reduce diuretic, natriuretic and antihypertensive effects of diuretics. (7)
- Dual inhibition of the renin-angiotensin system: Increased risk of renal impairment, hypotension, and hyperkalemia. (7)

8 USE IN SPECIFIC POPULATIONS

Lactation: Breastfeeding is not recommended. (8.2)

FULL PRESCRIBING INFORMATION

WARNING: FETAL TOXICITY

- When pregnancy is detected, discontinue Diovan HCT as soon as possible. (5.1)
- Drugs that act directly on the renin-angiotensin system can cause injury and death to the developing fetus. (5.1)

1 INDICATIONS AND USAGE

Diovan HCT (valsartan and hydrochlorothiazide, USP) is indicated for the treatment of hypertension, to lower blood pressure. Lowering blood pressure reduces the risk of fatal and nonfatal cardiovascular events, primarily strokes and myocardial infarctions. These benefits have been seen in controlled trials of antihypertensive drugs from a wide variety of pharmacologic classes, including hydrochlorothiazide and the angiotensin II receptor blocker (ARB) class to which valsartan principally belongs. There are no controlled trials demonstrating risk reduction with Diovan HCT.

Control of high blood pressure should be part of comprehensive cardiovascular risk management, including, as appropriate, lipid control, diabetes management, antithrombotic therapy, smoking cessation, exercise, and limited sodium intake. Many patients will require more than 1 drug to achieve blood pressure goals. For specific advice on goals and management, see published guidelines, such as those of the National High Blood Pressure Education Program’s Joint National Committee on Prevention, Detection, Evaluation, and Treatment of High Blood Pressure (JNC).

Numerous antihypertensive drugs, from a variety of pharmacologic classes and with different mechanisms of action, have been shown in randomized controlled trials to reduce cardiovascular morbidity and mortality, and it can be concluded that it is blood pressure reduction, and not some other pharmacologic property of the drugs, that is largely responsible for those benefits. The largest and most consistent cardiovascular outcome benefit has been a reduction in the risk of stroke, but reductions in myocardial infarction and cardiovascular mortality have also been seen regularly.

Elevated systolic or diastolic pressure causes increased cardiovascular risk, and the absolute risk increase per mmHg is greater at higher blood pressures, so that even modest reductions of severe hypertension can provide substantial benefit. Relative risk reduction from blood pressure reduction is similar across populations with varying absolute risk, so the absolute benefit is greater in patients who are at higher risk independent of their hypertension (e.g., patients with diabetes or hyperlipidemia), and such patients would be expected to benefit from more aggressive treatment to a lower blood pressure goal.

Some antihypertensive drugs have smaller blood pressure effects (as monotherapy) in black patients, and many antihypertensive drugs have additional approved indications and effects (e.g., on angina, heart failure, or diabetic kidney disease). These considerations may guide selection of therapy.

Add-On Therapy

Diovan HCT may be used in patients whose blood pressure is not adequately controlled on monotherapy.

Replacement Therapy

Diovan HCT may be substituted for the titrated components.

Initial Therapy

Diovan HCT may be used as initial therapy in patients who are likely to need multiple drugs to achieve blood pressure goals.

The choice of Diovan HCT as initial therapy for hypertension should be based on an assessment of potential benefits and risks.

Patients with stage 2 hypertension are at a relatively high risk for cardiovascular events (such as strokes, heart attacks, and heart failure), kidney failure, and vision problems, so prompt treatment is clinically relevant. The decision to use a combination as initial therapy should be individualized and should be shaped by considerations such as baseline blood pressure, the target goal, and the incremental likelihood of achieving goal with a combination compared to monotherapy. Individual blood pressure goals may vary based upon the patient’s risk.

Data from the high dose multifactorial trial [see Clinical Studies (14.1)] provides estimates of the probability of reaching a target blood pressure with Diovan HCT compared to valsartan or hydrochlorothiazide monotherapy. The figures below provide estimates of the likelihood of achieving systolic or diastolic blood pressure control with Diovan HCT 320/25 mg, based upon baseline systolic or diastolic blood pressure. The curve of each treatment group was estimated by logistic regression modeling. The estimated likelihood at the right tail of each curve is less reliable due to small numbers of subjects with high baseline blood pressures.

Figure 1: Probability of Achieving Systolic Blood Pressure < 140 mmHg at Week 8 | Figure 2: Probability of Achieving Diastolic Blood Pressure < 90 mmHg at Week 8
Figure 3: Probability of Achieving Systolic Blood Pressure < 130 mmHg at Week 8 | Figure 4: Probability of Achieving Diastolic Blood Pressure < 80 mmHg at Week 8

For example, a patient with a baseline blood pressure of 160/100 mmHg has about a 41% likelihood of achieving a goal of < 140 mmHg (systolic) and 60% likelihood of achieving < 90 mmHg (diastolic) on valsartan alone and the likelihood of achieving these goals on HCTZ alone is about 50% (systolic) or 57% (diastolic). The likelihood of achieving these goals on Diovan HCT rises to about 84% (systolic) or 80% (diastolic). The likelihood of achieving these goals on placebo is about 23% (systolic) or 36% (diastolic).

2 DOSAGE AND ADMINISTRATION

2.1 General Considerations

The usual starting dose is Diovan HCT 160/12.5 mg once daily. The dosage can be increased after 1 to 2 weeks of therapy to a maximum of one 320/25 tablet once daily as needed to control blood pressure [see Clinical Studies (14.2)]. Maximum antihypertensive effects are attained within 2 to 4 weeks after a change in dose.

2.2 Add-On Therapy

A patient whose blood pressure is not adequately controlled with valsartan (or another ARB) alone or hydrochlorothiazide alone may be switched to combination therapy with Diovan HCT.

A patient who experiences dose-limiting adverse reactions on either component alone may be switched to Diovan HCT containing a lower dose of that component in combination with the other to achieve similar blood pressure reductions. The clinical response to Diovan HCT should be subsequently evaluated and if blood pressure remains uncontrolled after 3 to 4 weeks of therapy, the dose may be titrated up to a maximum of 320/25 mg.

2.3 Replacement Therapy

Diovan HCT may be substituted for the titrated components.

2.4 Initial Therapy

Diovan HCT is not recommended as initial therapy in patients with intravascular volume depletion [see Warnings and Precautions (5.2)].

2.5 Use with Other Antihypertensive Drugs

Diovan HCT may be administered with other antihypertensive agents.

3 DOSAGE FORMS AND STRENGTHS

80/12.5 mg tablets, imprinted CG/HGH (Side 1/Side 2)

160/12.5 mg tablets, imprinted CG/HHH

160/25 mg tablets, imprinted NVR/HXH

320/12.5 mg tablets, imprinted NVR/HIL

320/25 mg tablets, imprinted NVR/CTI

4 CONTRAINDICATIONS

Diovan HCT (valsartan and hydrochlorothiazide, USP) is contraindicated in patients who are hypersensitive to any component of this product.

Because of the hydrochlorothiazide component, this product is contraindicated in patients with anuria or hypersensitivity to other sulfonamide-derived drugs.

Do not coadminister aliskiren with Diovan HCT in patients with diabetes [see Drug Interactions (7)].

5 WARNINGS AND PRECAUTIONS

5.1 Fetal Toxicity

Diovan HCT can cause fetal harm when administered to a pregnant woman. Use of drugs that act on the renin-angiotensin system during the second and third trimesters of pregnancy reduces fetal renal function and increases fetal and neonatal morbidity and death. Resulting oligohydramnios can be associated with fetal lung hypoplasia and skeletal deformations. Potential neonatal adverse effects include skull hypoplasia, anuria, hypotension, renal failure, and death.

Thiazides cross the placenta, and use of thiazides during pregnancy is associated with fetal or neonatal jaundice, thrombocytopenia, and possibly other adverse reactions that have occurred in adults.

When pregnancy is detected, discontinue Diovan HCT as soon as possible [see Use in Specific Populations (8.1)].

5.2 Hypotension in Volume- and/or Salt-Depleted Patients

Excessive reduction of blood pressure was rarely seen (0.7%) in patients with uncomplicated hypertension treated with Diovan HCT in controlled trials. In patients with an activated renin-angiotensin system, such as volume- and/or salt-depleted patients receiving high doses of diuretics, symptomatic hypotension may occur. This condition should be corrected prior to administration of Diovan HCT, or the treatment should start under close medical supervision.

If hypotension occurs, place the patient in the supine position and, if necessary, give intravenous normal saline. A transient hypotensive response is not a contraindication to further treatment, which usually can be continued without difficulty once the blood pressure has stabilized.

5.3 Impaired Renal Function

Changes in renal function including acute renal failure can be caused by drugs that inhibit the renin-angiotensin system and by diuretics. Patients whose renal function may depend in part on the activity of the renin-angiotensin system (e.g., patients with renal artery stenosis, chronic kidney disease, severe congestive heart failure, or volume depletion) may be at particular risk of developing acute renal failure on Diovan HCT. Monitor renal function periodically in these patients. Consider withholding or discontinuing therapy in patients who develop a clinically significant decrease in renal function on Diovan HCT [see Drug Interactions (7)].

5.4 Hypersensitivity Reaction

Hypersensitivity reactions to hydrochlorothiazide may occur in patients with or without a history of allergy or bronchial asthma, but are more likely in patients with such a history.

5.5 Systemic Lupus Erythematosus

Thiazide diuretics have been reported to cause exacerbation or activation of systemic lupus erythematosus.

5.6 Lithium Interaction

Increases in serum lithium concentrations and lithium toxicity have been reported with concomitant use of valsartan or thiazide diuretics. Monitor lithium levels in patients receiving Diovan HCT and lithium [see Drug Interactions (7)].

5.7 Potassium Abnormalities

In the controlled trials of various doses of Diovan HCT, the incidence of hypertensive patients who developed hypokalemia (serum potassium < 3.5 mEq/L) was 3.0%; the incidence of hyperkalemia (serum potassium > 5.7 mEq/L) was 0.4%.

Hydrochlorothiazide can cause hypokalemia and hyponatremia. Hypomagnesemia can result in hypokalemia which appears difficult to treat despite potassium repletion. Drugs that inhibit the renin-angiotensin system can cause hyperkalemia. Monitor serum electrolytes periodically.

If hypokalemia is accompanied by clinical signs (e.g., muscular weakness, paresis, or ECG alterations), Diovan HCT should be discontinued. Correction of hypokalemia and any coexisting hypomagnesemia is recommended prior to the initiation of thiazides.

Some patients with heart failure have developed increases in potassium with Diovan therapy. These effects are usually minor and transient, and they are more likely to occur in patients with pre-existing renal impairment. Dosage reduction and/or discontinuation of the diuretic and/or Diovan may be required [see Adverse Reactions (6.1)].

5.8 Acute Myopia and Secondary Angle-Closure Glaucoma

Hydrochlorothiazide, a sulfonamide, can cause an idiosyncratic reaction, resulting in acute transient myopia and acute angle-closure glaucoma. Symptoms include acute onset of decreased visual acuity or ocular pain and typically occur within hours to weeks of drug initiation. Untreated acute angle-closure glaucoma can lead to permanent vision loss. The primary treatment is to discontinue hydrochlorothiazide as rapidly as possible. Prompt medical or surgical treatments may need to be considered if the intraocular pressure remains uncontrolled. Risk factors for developing acute angle-closure glaucoma may include a history of sulfonamide or penicillin allergy.

5.9 Metabolic Disturbances

Hydrochlorothiazide may alter glucose tolerance and raise serum levels of cholesterol and triglycerides.

Hydrochlorothiazide may raise the serum uric acid level due to reduced clearance of uric acid and may cause or exacerbate hyperuricemia and precipitate gout in susceptible patients.

Hydrochlorothiazide decreases urinary calcium excretion and may cause elevations of serum calcium. Monitor calcium levels in patients with hypercalcemia receiving Diovan HCT.

6 ADVERSE REACTIONS

6.1 Clinical Trials Experience

Because clinical studies are conducted under widely varying conditions, adverse reactions rates observed in the clinical studies of a drug cannot be directly compared to rates in the clinical studies of another drug and may not reflect the rates observed in practice. The adverse reaction information from clinical trials does, however, provide a basis for identifying the adverse events that appear to be related to drug use and for approximating rates.

Hypertension

Diovan HCT (valsartan and hydrochlorothiazide, USP) has been evaluated for safety in more than 5700 patients, including over 990 treated for over 6 months, and over 370 for over 1 year. Adverse experiences have generally been mild and transient in nature and have only infrequently required discontinuation of therapy. The overall incidence of adverse reactions with Diovan HCT was comparable to placebo.

The overall frequency of adverse reactions was neither dose-related nor related to gender, age, or race. In controlled clinical trials, discontinuation of therapy due to side effects was required in 2.3% of valsartan-hydrochlorothiazide patients and 3.1% of placebo patients. The most common reasons for discontinuation of therapy with Diovan HCT were headache and dizziness.

The only adverse reaction that occurred in controlled clinical trials in at least 2% of patients treated with Diovan HCT and at a higher incidence in valsartan-hydrochlorothiazide (n = 4372) than placebo (n = 262) patients was nasopharyngitis (2.4% vs. 1.9%).

Dose-related orthostatic effects were seen in fewer than 1% of patients. In individual trials, a dose-related increase in the incidence of dizziness was observed in patients treated with Diovan HCT.

Initial Therapy-Hypertension

In a clinical study in patients with severe hypertension (diastolic blood pressure ≥ 110 mmHg and systolic blood pressure ≥ 140 mmHg), the overall pattern of adverse reactions reported through 6 weeks of follow-up was similar in patients treated with Diovan HCT as initial therapy and in patients treated with valsartan as initial therapy. Comparing the groups treated with Diovan HCT (force-titrated to 320/25 mg) and valsartan (force-titrated to 320 mg), dizziness was observed in 6% and 2% of patients, respectively. Hypotension was observed in 1% of those patients receiving Diovan HCT and 0% of patients receiving valsartan. There were no reported cases of syncope in either treatment group. Laboratory changes with Diovan HCT as initial therapy in patients with severe hypertension were similar to those reported with Diovan HCT in patients with less severe hypertension [see Clinical Studies (14.2), Drug Interactions (7)].

Valsartan: In trials in which valsartan was compared to an ACE inhibitor with or without placebo, the incidence of dry cough was significantly greater in the ACE inhibitor group (7.9%) than in the groups who received valsartan (2.6%) or placebo (1.5%). In a 129-patient trial limited to patients who had had dry cough when they had previously received ACE inhibitors, the incidences of cough in patients who received valsartan, hydrochlorothiazide, or lisinopril were 20%, 19%, 69%, respectively (p < 0.001).

6.2 Postmarketing Experience

The following additional adverse reactions have been reported in valsartan or valsartan/hydrochlorothiazide postmarketing experience. Because these reactions are reported voluntarily from a population of uncertain size, it is not always possible to reliably estimate their frequency or establish a causal relationship to drug exposure.

Hypersensitivity: Angioedema has been reported. Some of these patients previously experienced angioedema with other drugs including ACE inhibitors. Diovan HCT should not be re-administered to patients who have had angioedema.

Digestive: Elevated liver enzymes and reports of hepatitis

Musculoskeletal: Rhabdomyolysis

Renal: Impaired renal function

Dermatologic: Alopecia, bullous dermatitis

Vascular: Vasculitis

Nervous System: Syncope

Hydrochlorothiazide:

The following additional adverse reactions have been reported in postmarketing experience with hydrochlorothiazide:

Acute renal failure, renal disorder, aplastic anemia, erythema multiforme, pyrexia, muscle spasm, asthenia, acute angle-closure glaucoma, bone marrow failure, worsening of diabetes control, hypokalemia, blood lipids increased, hyponatremia, hypomagnesemia, hypercalcemia, hypochloremic alkalosis, impotence, and visual impairment.

Pathological changes in the parathyroid gland of patients with hypercalcemia and hypophosphatemia have been observed in a few patients on prolonged thiazide therapy. If hypercalcemia occurs, further diagnostic evaluation is necessary.

Non-melanoma Skin Cancer: Hydrochlorothiazide is associated with an increased risk of non-melanoma skin cancer. In a study conducted in the Sentinel System, increased risk was predominantly for squamous cell carcinoma (SCC) and in white patients taking large cumulative doses. The increased risk for SCC in the overall population was approximately 1 additional case per 16,000 patients per year, and for white patients taking a cumulative dose of ≥ 50,000 mg the risk increase was approximately 1 additional SCC case for every 6,700 patients per year.

7 DRUG INTERACTIONS

Valsartan-Hydrochlorothiazide:

Lithium: Increases in serum lithium concentrations and lithium toxicity have been reported during concomitant administration of lithium with angiotensin II receptor antagonists or thiazides. Monitor lithium levels in patients taking Diovan HCT.

Valsartan:

Agents Increasing Serum Potassium: Concomitant use of valsartan with other agents that block the renin-angiotensin system, potassium-sparing diuretics (e.g., spironolactone, triamterene, amiloride), potassium supplements, salt substitutes containing potassium or other drugs that may increase potassium levels (e.g., heparin) may lead to increases in serum potassium and in heart failure patients to increases in serum creatinine. If co-medication is considered necessary, monitoring of serum potassium is advisable.

Non-Steroidal Anti-Inflammatory Agents (NSAIDs), Including Selective Cyclooxygenase-2 Inhibitors (COX-2 Inhibitors): In patients who are elderly, volume-depleted (including those on diuretic therapy), or with compromised renal function, coadministration of NSAIDs, including selective COX-2 inhibitors, with angiotensin II receptor antagonists, including valsartan, may result in deterioration of renal function, including possible acute renal failure. These effects are usually reversible. Monitor renal function periodically in patients receiving valsartan and NSAID therapy.

The antihypertensive effect of angiotensin II receptor antagonists, including valsartan, may be attenuated by NSAIDs including selective COX-2 inhibitors.

Dual Blockade of the Renin-Angiotensin System (RAS): Dual blockade of the RAS with angiotensin receptor blockers, ACE inhibitors, or aliskiren is associated with increased risks of hypotension, hyperkalemia, and changes in renal function (including acute renal failure) compared to monotherapy. Most patients receiving the combination of two RAS inhibitors do not obtain any additional benefit compared to monotherapy. In general, avoid combined use of RAS inhibitors. Closely monitor blood pressure, renal function and electrolytes in patients on valsartan and other agents that affect the RAS.

Do not coadminister aliskiren with valsartan in patients with diabetes. Avoid use of aliskiren with valsartan in patients with renal impairment (GFR < 60 mL/min).

Hydrochlorothiazide: When administered concurrently, the following drugs may interact with thiazide diuretics:

Antidiabetic Drugs (oral agents and insulin) - Dosage adjustment of the antidiabetic drug may be required.

Nonsteroidal Anti-inflammatory Drugs (NSAIDs and COX-2 selective inhibitors) - When Diovan HCT and nonsteroidal anti-inflammatory agents are used concomitantly, the patient should be observed closely to determine if the desired effect of the diuretic is obtained.

Carbamazepine – May lead to symptomatic hyponatremia.

Ion Exchange Resins: Staggering the dosage of hydrochlorothiazide and ion exchange resins (e.g., cholestyramine, colestipol) such that hydrochlorothiazide is administered at least 4 hours before or 4 to 6 hours after the administration of resins would potentially minimize the interaction [see Clinical Pharmacology (12.3)].

Cyclosporine: Concomitant treatment with cyclosporine may increase the risk of hyperuricemia and gout-type complications.

8 USE IN SPECIFIC POPULATIONS

8.1 Pregnancy

Risk Summary

Diovan HCT can cause fetal harm when administered to a pregnant woman. Use of drugs that act on the renin-angiotensin system during the second and third trimesters of pregnancy reduces fetal renal function and increases fetal and neonatal morbidity and death. Most epidemiologic studies examining fetal abnormalities after exposure to antihypertensive use in the first trimester have not distinguished drugs affecting the renin-angiotensin system from other antihypertensive agents. Published reports include cases of anhydramnios and oligohydramnios in pregnant women treated with valsartan (see Clinical Considerations).

When pregnancy is detected discontinue Diovan HCT as soon as possible.

The estimated background risk of major birth defects and miscarriage for the indicated population is unknown. All pregnancies have a background risk of birth defect, loss, or other adverse outcomes. In the U.S. general population, the estimated background risk of major birth defects and miscarriage in clinically recognized pregnancies is 2-4% and 15-20%, respectively.

Clinical Considerations

Disease-associated maternal and/or embryo/fetal risk

Hypertension in pregnancy increases the maternal risk for pre-eclampsia, gestational diabetes, premature delivery, and delivery complications (e.g., need for cesarean section and post-partum hemorrhage). Hypertension increases the fetal risk for intrauterine growth restriction and intrauterine death. Pregnant women with hypertension should be carefully monitored and managed accordingly.

Fetal/Neonatal Adverse Reactions

Valsartan

Oligohydramnios in pregnant women who use drugs affecting the renin-angiotensin system in the second and third trimesters of pregnancy can result in the following: reduced fetal renal function leading to anuria and renal failure, fetal lung hypoplasia, skeletal deformations, including skull hypoplasia, hypotension and death.

Perform serial ultrasound examinations to assess the intra-amniotic environment. Fetal testing may be appropriate, based on the week of gestation. Patients and physicians should be aware, however, that oligohydramnios may not appear until after the fetus has sustained irreversible injury. If oligohydramnios is observed, consider alternative drug treatment. Closely observe neonates with histories of in utero exposure to Diovan HCT for hypotension, oliguria, and hyperkalemia. In neonates with a history of in utero exposure to Diovan HCT, if oliguria or hypotension occurs, support blood pressure and renal perfusion. Exchange transfusions or dialysis may be required as a means of reversing hypotension and replacing renal function.

Hydrochlorothiazide

Thiazides can cross the placenta, and concentrations reached in the umbilical vein approach those in the maternal plasma. Hydrochlorothiazide, like other diuretics, can cause placental hypoperfusion. It accumulates in the amniotic fluid, with reported concentrations up to 19 times higher than in umbilical vein plasma. Use of thiazides during pregnancy is associated with a risk of fetal or neonatal jaundice or thrombocytopenia. Since they do not prevent or alter the course of EPH (Edema, Proteinuria, Hypertension) gestosis (pre-eclampsia), these drugs should not be used to treat hypertension in pregnant women. The use of hydrochlorothiazide for other indications (e.g., heart disease) in pregnancy should be avoided.

Data

Animal Data

Valsartan plus Hydrochlorothiazide

There was no evidence of teratogenicity in mice, rats, or rabbits treated orally with valsartan at doses of up to 600, 100, and 10 mg/kg/day [9, 3.5 and 0.5 times the maximum recommended human dose (MRHD)], respectively, in combination with hydrochlorothiazide at doses up to 188, 31, and 3 mg/kg/day (38, 13 and 2 times the MRHD).

Fetotoxicity was observed in association with maternal toxicity in rats at valsartan/hydrochlorothiazide doses of ≥ 200/63 mg/kg/day and in rabbits at valsartan/hydrochlorothiazide doses of 10/3 mg/kg/day. Evidence of fetotoxicity in rats consisted of decreased fetal weight and fetal variations of sternebrae, vertebrae, ribs, and/or renal papillae. Evidence of fetotoxicity in rabbits included increased numbers of late resorptions with resultant increases in total resorptions, post-implantation losses, and decreased number of live fetuses.

8.2 Lactation

Risk Summary

There is limited information regarding the presence of Diovan HCT in human milk, the effects on the breastfed infant, or the effects on milk production. Valsartan is present in rat milk. Hydrochlorothiazide is present in human breast milk. Because of the potential for serious adverse reactions in breastfed infants, advise a nursing woman that breastfeeding is not recommended during treatment with Diovan HCT.

Data

Valsartan was detected in the milk of lactating rats 15 minutes after oral administration of a 3 mg/kg dose.

8.4 Pediatric Use

Safety and effectiveness of Diovan HCT in pediatric patients have not been established.

8.5 Geriatric Use

In the controlled clinical trials of Diovan HCT, 764 (17.5%) patients treated with valsartan-hydrochlorothiazide were ≥ 65 years and 118 (2.7%) were ≥ 75 years. No overall difference in the efficacy or safety of valsartan-hydrochlorothiazide was observed between these patients and younger patients, but greater sensitivity of some older individuals cannot be ruled out.

8.6 Renal Impairment

Safety and effectiveness of Diovan HCT in patients with severe renal impairment (CrCl ≤ 30 mL/min) have not been established. No dose adjustment is required in patients with mild (CrCl 60 to 90 mL/min) or moderate (CrCl 30 to 60 mL/min) renal impairment.

8.7 Hepatic Impairment

Valsartan

No dose adjustment is necessary for patients with mild-to-moderate liver disease. No dosing recommendations can be provided for patients with severe liver disease.

Hydrochlorothiazide

Minor alterations of fluid and electrolyte balance may precipitate hepatic coma in patients with impaired hepatic function or progressive liver disease.

10 OVERDOSAGE

Limited data are available related to overdosage in humans. The most likely manifestations of overdosage would be hypotension and tachycardia; bradycardia could occur from parasympathetic (vagal) stimulation. Depressed level of consciousness, circulatory collapse and shock have been reported. If symptomatic hypotension should occur institute supportive treatment.

Valsartan is not removed from the plasma by dialysis.

The degree to which hydrochlorothiazide is removed by hemodialysis has not been established. The most common signs and symptoms observed in patients are those caused by electrolyte depletion (hypokalemia, hypochloremia, hyponatremia) and dehydration resulting from excessive diuresis. If digitalis has also been administered, hypokalemia may accentuate cardiac arrhythmias.

In rats and marmosets, single oral doses of valsartan up to 1524 and 762 mg/kg in combination with hydrochlorothiazide at doses up to 476 and 238 mg/kg, respectively, did not show any adverse treatment-related effects. These no adverse effect doses in rats and marmosets, respectively, represent 46.5 and 23 times the MRHD of valsartan and 188 and 113 times the MRHD of hydrochlorothiazide on a mg/m^2 basis (Calculations assume an oral dose of 320 mg/day valsartan in combination with 25 mg/day hydrochlorothiazide and a 60-kg patient.)

Valsartan was without grossly observable adverse effects at single oral doses up to 2,000 mg/kg in rats and up to 1,000 mg/kg in marmosets, except for salivation and diarrhea in the rat and vomiting in the marmoset at the highest dose (60 and 31 times, respectively, the MRHD on a mg/m^2 basis) (Calculations assume an oral dose of 320 mg/day and a 60-kg patient).

The oral LD50 of hydrochlorothiazide is greater than 10 g/kg in both mice and rats, which represents 2027 and 4054 times, respectively, the MRHD on a mg/m^2 basis (Calculations assume an oral dose of 25 mg/day and a 60-kg patient.)

11 DESCRIPTION

Diovan HCT (valsartan and hydrochlorothiazide, USP) is a combination of valsartan, an orally active, specific angiotensin II receptor blocker (ARB) acting on the AT1 receptor subtype, and hydrochlorothiazide, a diuretic.

Valsartan, a nonpeptide molecule, is chemically described as N-(1-oxopentyl)-N-[[2′-(1H-tetrazol-5-yl)[1,1′-biphenyl]-4-yl]methyl]-L-Valine. Its empirical formula is C24H29N5O3, its molecular weight is 435.5, and its structural formula is:

Valsartan is a white to practically white fine powder. It is soluble in ethanol and methanol and slightly soluble in water.

Hydrochlorothiazide, USP is a white, or practically white, practically odorless, crystalline powder. It is slightly soluble in water; freely soluble in sodium hydroxide solution, in n-butylamine, and in dimethylformamide; sparingly soluble in methanol; and insoluble in ether, in chloroform, and in dilute mineral acids. Hydrochlorothiazide is chemically described as 6-chloro-3,4-dihydro-2H-1,2,4-benzothiadiazine-7-sulfonamide 1,1-dioxide.

Hydrochlorothiazide is a thiazide diuretic. Its empirical formula is C7H8ClN3O4S2, its molecular weight is 297.73, and its structural formula is:

Diovan HCT tablets are formulated for oral administration to contain valsartan and hydrochlorothiazide, USP 80/12.5 mg, 160/12.5 mg, 160/25 mg, 320/12.5 mg, and 320/25 mg. The inactive ingredients of the tablets are colloidal silicon dioxide, crospovidone, hydroxypropyl methylcellulose, iron oxides, magnesium stearate, microcrystalline cellulose, polyethylene glycol, talc, and titanium dioxide.

12 CLINICAL PHARMACOLOGY

12.1 Mechanism of Action

Angiotensin II is formed from angiotensin I in a reaction catalyzed by angiotensin-converting enzyme (ACE, kininase II). Angiotensin II is the principal pressor agent of the renin-angiotensin system, with effects that include vasoconstriction, stimulation of synthesis and release of aldosterone, cardiac stimulation, and renal reabsorption of sodium. Valsartan blocks the vasoconstrictor and aldosterone-secreting effects of angiotensin II by selectively blocking the binding of angiotensin II to the AT1 receptor in many tissues, such as vascular smooth muscle and the adrenal gland. Its action is therefore independent of the pathways for angiotensin II synthesis.

There is also an AT2 receptor found in many tissues, but AT2 is not known to be associated with cardiovascular homeostasis. Valsartan has much greater affinity (about 20,000-fold) for the AT1 receptor than for the AT2 receptor. The primary metabolite of valsartan is essentially inactive with an affinity for the AT1 receptor about one 200th that of valsartan itself.

Blockade of the renin-angiotensin system with ACE inhibitors, which inhibit the biosynthesis of angiotensin II from angiotensin I, is widely used in the treatment of hypertension. ACE inhibitors also inhibit the degradation of bradykinin, a reaction also catalyzed by ACE. Because valsartan does not inhibit ACE (kininase II), it does not affect the response to bradykinin. Whether this difference has clinical relevance is not yet known. Valsartan does not bind to or block other hormone receptors or ion channels known to be important in cardiovascular regulation.

Blockade of the angiotensin II receptor inhibits the negative regulatory feedback of angiotensin II on renin secretion, but the resulting increased plasma renin activity and angiotensin II circulating levels do not overcome the effect of valsartan on blood pressure.

Hydrochlorothiazide is a thiazide diuretic. Thiazides affect the renal tubular mechanisms of electrolyte reabsorption, directly increasing excretion of sodium and chloride in approximately equivalent amounts. Indirectly, the diuretic action of hydrochlorothiazide reduces plasma volume, with consequent increases in plasma renin activity, increases in aldosterone secretion, increases in urinary potassium loss, and decreases in serum potassium. The renin-aldosterone link is mediated by angiotensin II, so coadministration of an angiotensin II receptor antagonist tends to reverse the potassium loss associated with these diuretics.

The mechanism of the antihypertensive effect of thiazides is unknown.

12.2 Pharmacodynamics

Valsartan: Valsartan inhibits the pressor effect of angiotensin II infusions. An oral dose of 80 mg inhibits the pressor effect by about 80% at peak with approximately 30% inhibition persisting for 24 hours. No information on the effect of larger doses is available.

Removal of the negative feedback of angiotensin II causes a 2- to 3-fold rise in plasma renin and consequent rise in angiotensin II plasma concentration in hypertensive patients. Minimal decreases in plasma aldosterone were observed after administration of valsartan; very little effect on serum potassium was observed.

Hydrochlorothiazide: After oral administration of hydrochlorothiazide, diuresis begins within 2 hours, peaks in about 4 hours and lasts about 6 to 12 hours.

Pharmacodynamic Drug Interactions

Hydrochlorothiazide:

Alcohol, barbiturates, or narcotics: Potentiation of orthostatic hypotension may occur.

Skeletal muscle relaxants: Possible increased responsiveness to muscle relaxants such as curare derivatives.

Digitalis glycosides: Thiazide-induced hypokalemia or hypomagnesemia may predispose the patient to digoxin toxicity.

12.3 Pharmacokinetics

Valsartan: Valsartan peak plasma concentration is reached 2 to 4 hours after dosing. Valsartan shows bi-exponential decay kinetics following intravenous administration, with an average elimination half-life of about 6 hours. Absolute bioavailability for the capsule formulation is about 25% (range 10% to 35%). Food decreases the exposure (as measured by area under the curve [AUC]) to valsartan by about 40% and peak plasma concentration (Cmax) by about 50%. AUC and Cmax values of valsartan increase approximately linearly with increasing dose over the clinical dosing range. Valsartan does not accumulate appreciably in plasma following repeated administration.

Hydrochlorothiazide: The estimated absolute bioavailability of hydrochlorothiazide after oral administration is about 70%. Peak plasma hydrochlorothiazide concentrations (Cmax) are reached within 2 to 5 hours after oral administration. There is no clinically significant effect of food on the bioavailability of hydrochlorothiazide.

Hydrochlorothiazide binds to albumin (40% to 70%) and distributes into erythrocytes. Following oral administration, plasma hydrochlorothiazide concentrations decline bi-exponentially, with a mean distribution half-life of about 2 hours and an elimination half-life of about 10 hours.

Diovan HCT: Diovan HCT may be administered with or without food.

Distribution

Valsartan: The steady state volume of distribution of valsartan after intravenous administration is small (17 L), indicating that valsartan does not distribute into tissues extensively. Valsartan is highly bound to serum proteins (95%), mainly serum albumin.

Metabolism

Valsartan: The primary metabolite, accounting for about 9% of dose, is valeryl 4-hydroxy valsartan. In vitro metabolism studies involving recombinant CYP 450 enzymes indicated that the CYP 2C9 isoenzyme is responsible for the formation of valeryl-4-hydroxy valsartan. Valsartan does not inhibit CYP 450 isozymes at clinically relevant concentrations. CYP 450 mediated drug interaction between valsartan and coadministered drugs are unlikely because of the low extent of metabolism.

Hydrochlorothiazide: Is not metabolized.

Excretion

Valsartan: Valsartan, when administered as an oral solution, is primarily recovered in feces (about 83% of dose) and urine (about 13% of dose). The recovery is mainly as unchanged drug, with only about 20% of dose recovered as metabolites.

Following intravenous administration, plasma clearance of valsartan is about 2 L/h and its renal clearance is 0.62 L/h (about 30% of total clearance).

Hydrochlorothiazide: About 70% of an orally administered dose of hydrochlorothiazide is eliminated in the urine as unchanged drug.

Specific Populations

Geriatric: Exposure (measured by AUC) to valsartan is higher by 70% and the half-life is longer by 35% in the elderly than in the young. A limited amount of data suggest that the systemic clearance of hydrochlorothiazide is reduced in both healthy and hypertensive elderly subjects compared to young healthy volunteers.

Gender: Pharmacokinetics of valsartan do not differ significantly between males and females.

Race: Pharmacokinetic differences due to race have not been studied.

Renal Insufficiency: There is no apparent correlation between renal function (measured by creatinine clearance) and exposure (measured by AUC) to valsartan in patients with different degrees of renal impairment. Valsartan has not been studied in patients with severe impairment of renal function (creatinine clearance < 10 mL/min). Valsartan is not removed from the plasma by hemodialysis.

In a study in individuals with impaired renal function, the mean elimination half-life of hydrochlorothiazide was doubled in individuals with mild/moderate renal impairment (30 < CrCl < 90 mL/min) and tripled in severe renal impairment (CrCl ≤ 30 mL/min), compared to individuals with normal renal function (CrCl > 90 mL/min) [see Use in Specific Populations (8.6)].

Hepatic Insufficiency: On average, patients with mild-to-moderate chronic liver disease have twice the exposure (measured by AUC values) to valsartan of healthy volunteers (matched by age, sex, and weight) [see Use in Specific Populations (8.7)].

Drug Interactions

Valsartan

No clinically significant pharmacokinetic interactions were observed when Diovan (valsartan) was coadministered with amlodipine, atenolol, cimetidine, digoxin, furosemide, glyburide, hydrochlorothiazide, or indomethacin. The valsartan-atenolol combination was more antihypertensive than either component, but it did not lower the heart rate more than atenolol alone.

Coadministration of valsartan and warfarin did not change the pharmacokinetics of valsartan or the time-course of the anticoagulant properties of warfarin.

Transporters: The results from an in vitro study with human liver tissue indicate that valsartan is a substrate of the hepatic uptake transporter OATP1B1 and the hepatic efflux transporter MRP2. Coadministration of inhibitors of the uptake transporter (rifampin, cyclosporine) or efflux transporter (ritonavir) may increase the systemic exposure to valsartan.

Hydrochlorothiazide:

Drugs that alter gastrointestinal motility: The bioavailability of thiazide-type diuretics may be increased by anticholinergic agents (e.g., atropine, biperiden), apparently due to a decrease in gastrointestinal motility and the stomach emptying rate. Conversely, pro-kinetic drugs may decrease the bioavailability of thiazide diuretics.

Cholestyramine: In a dedicated drug interaction study, administration of cholestyramine 2 hours before hydrochlorothiazide resulted in a 70% reduction in exposure to hydrochlorothiazide. Further, administration of hydrochlorothiazide 2 hours before cholestyramine resulted in 35% reduction in exposure to hydrochlorothiazide.

Antineoplastic agents (e.g., cyclophosphamide, methotrexate): Concomitant use of thiazide diuretics may reduce renal excretion of cytotoxic agents and enhance their myelosuppressive effects.

13 NONCLINICAL TOXICOLOGY

13.1 Carcinogenesis, Mutagenesis, Impairment of Fertility

Valsartan-Hydrochlorothiazide: No carcinogenicity, mutagenicity, or fertility studies have been conducted with the combination of valsartan and hydrochlorothiazide. However, these studies have been conducted for valsartan as well as hydrochlorothiazide alone. Based on the preclinical safety and human pharmacokinetic studies, there is no indication of any adverse interaction between valsartan and hydrochlorothiazide.

Valsartan: There was no evidence of carcinogenicity when valsartan was administered in the diet to mice and rats for up to 2 years at doses up to 160 and 200 mg/kg/day, respectively. These doses in mice and rats are about 2.6 and 6 times, respectively, the MRHD on a mg/m^2 basis (Calculations assume an oral dose of 320 mg/day and a 60-kg patient).

Mutagenicity assays did not reveal any valsartan-related effects at either the gene or chromosome level. These assays included bacterial mutagenicity tests with Salmonella (Ames) and E. coli; a gene mutation test with Chinese hamster V79 cells; a cytogenetic test with Chinese hamster ovary cells; and a rat micronucleus test.

Valsartan had no adverse effects on the reproductive performance of male or female rats at oral doses up to 200 mg/kg/day. This dose is about 6 times the MRHD on a mg/m^2 basis (Calculations assume an oral dose of 320 mg/day and a 60-kg patient).

Hydrochlorothiazide: Two-year feeding studies in mice and rats conducted under the auspices of the National Toxicology Program (NTP) uncovered no evidence of a carcinogenic potential of hydrochlorothiazide in female mice (at doses of up to approximately 600 mg/kg/day) or in male and female rats (at doses of up to approximately 100 mg/kg/day). The NTP, however, found equivocal evidence for hepatocarcinogenicity in male mice.

Hydrochlorothiazide was not genotoxic in vitro in the Ames mutagenicity assay of Salmonella typhimurium strains TA 98, TA 100, TA 1535, TA 1537, and TA 1538 and in the Chinese Hamster Ovary (CHO) test for chromosomal aberrations, or in vivo in assays using mouse germinal cell chromosomes, Chinese hamster bone marrow chromosomes, and the Drosophila sex-linked recessive lethal trait gene. Positive test results were obtained only in the in vitro CHO Sister Chromatid Exchange (clastogenicity) and in the Mouse Lymphoma Cell (mutagenicity) assays, using concentrations of hydrochlorothiazide from 43 to 1300 mcg/mL, and in the Aspergillus Nidulans non-disjunction assay at an unspecified concentration.

Hydrochlorothiazide had no adverse effects on the fertility of mice and rats of either sex in studies wherein these species were exposed, via their diet, to doses of up to 100 and 4 mg/kg, respectively, prior to mating and throughout gestation. These doses of hydrochlorothiazide in mice and rats represent 19 and 1.5 times, respectively, the MRHD on a mg/m^2 basis. (Calculations assume an oral dose of 25 mg/day and a 60-kg patient.)

14 CLINICAL STUDIES

14.1 Hypertension

Valsartan-Hydrochlorothiazide: In controlled clinical trials including over 7600 patients, 4372 patients were exposed to valsartan (80, 160, and 320 mg) and concomitant hydrochlorothiazide (12.5 and 25 mg). Two factorial trials compared various combinations of 80/12.5 mg, 80/25 mg, 160/12.5 mg, 160/25 mg, 320/12.5 mg, and 320/25 mg with their respective components and placebo. The combination of valsartan and hydrochlorothiazide resulted in additive placebo-adjusted decreases in systolic and diastolic blood pressure at trough of 14-21/8-11 mmHg at 80/12.5 mg to 320/25 mg, compared to 7-10/4-5 mmHg for valsartan 80 mg to 320 mg, and 5-11/2-5 mmHg for hydrochlorothiazide 12.5 mg to 25 mg alone.

Three other controlled trials investigated the addition of hydrochlorothiazide to patients who did not respond adequately to valsartan 80 mg to valsartan 320 mg, resulted in the additional lowering of systolic and diastolic blood pressure by approximately 4-12/2-5 mmHg.

The maximal antihypertensive effect was attained 4 weeks after the initiation of therapy, the first time point at which blood pressure was measured in these trials.

In long-term follow-up studies (without placebo control), the effect of the combination of valsartan and hydrochlorothiazide appeared to be maintained for up to 2 years. The antihypertensive effect is independent of age or gender. The overall response to the combination was similar for black and non-black patients.

There was essentially no change in heart rate in patients treated with the combination of valsartan and hydrochlorothiazide in controlled trials.

There are no trials of the Diovan HCT combination tablet demonstrating reductions in cardiovascular risk in patients with hypertension, but the hydrochlorothiazide component and several ARBs, which are the same pharmacological class as the valsartan component, have demonstrated such benefits.

Valsartan: The antihypertensive effects of valsartan were demonstrated principally in 7 placebo-controlled, 4- to 12-week trials (1 in patients over 65 years) of dosages from 10 to 320 mg/day in patients with baseline diastolic blood pressures of 95-115 mmHg. The studies allowed comparison of once-daily and twice-daily regimens of 160 mg/day; comparison of peak and trough effects; comparison (in pooled data) of response by gender, age, and race; and evaluation of incremental effects of hydrochlorothiazide.

Administration of valsartan to patients with essential hypertension results in a significant reduction of sitting, supine, and standing systolic and diastolic blood pressure, usually with little or no orthostatic change.

In most patients, after administration of a single oral dose, onset of antihypertensive activity occurs at approximately 2 hours, and maximum reduction of blood pressure is achieved within 6 hours. The antihypertensive effect persists for 24 hours after dosing, but there is a decrease from peak effect at lower doses (40 mg) presumably reflecting loss of inhibition of angiotensin II. At higher doses, however (160 mg), there is little difference in peak and trough effect. During repeated dosing, the reduction in blood pressure with any dose is substantially present within 2 weeks, and maximal reduction is generally attained after 4 weeks. In long-term follow-up studies (without placebo control), the effect of valsartan appeared to be maintained for up to 2 years. The antihypertensive effect is independent of age, gender or race. The latter finding regarding race is based on pooled data and should be viewed with caution, because antihypertensive drugs that affect the renin-angiotensin system (that is, ACE inhibitors and angiotensin II blockers) have generally been found to be less effective in low-renin hypertensives (frequently blacks) than in high-renin hypertensives (frequently whites). In pooled, randomized, controlled trials of Diovan that included a total of 140 blacks and 830 whites, valsartan and an ACE-inhibitor control were generally at least as effective in blacks as whites. The explanation for this difference from previous findings is unclear.

Abrupt withdrawal of valsartan has not been associated with a rapid increase in blood pressure.

The 7 studies of valsartan monotherapy included over 2000 patients randomized to various doses of valsartan and about 800 patients randomized to placebo. Doses below 80 mg were not consistently distinguished from those of placebo at trough, but doses of 80, 160 and 320 mg produced dose-related decreases in systolic and diastolic blood pressure, with the difference from placebo of approximately 6-9/3-5 mmHg at 80 to 160 mg and 9/6 mmHg at 320 mg.

Patients with an inadequate response to 80 mg once daily were titrated to either 160 mg once daily or 80 mg twice daily, which resulted in a similar response in both groups.

In another 4-week study, 1876 patients randomized to valsartan 320 mg once daily had an incremental blood pressure reduction 3/1 mmHg lower than did 1900 patients randomized to valsartan 160 mg once daily.

In controlled trials, the antihypertensive effect of once daily valsartan 80 mg was similar to that of once daily enalapril 20 mg or once daily lisinopril 10 mg.

There was essentially no change in heart rate in valsartan-treated patients in controlled trials.

14.2 Initial Therapy - Hypertension

The safety and efficacy of Diovan HCT as initial therapy for patients with severe hypertension (defined as a sitting diastolic blood pressure ≥ 110 mmHg and systolic blood pressure ≥ 140 mmHg off all antihypertensive therapy) were studied in a 6-week multicenter, randomized, double-blind study. Patients were randomized to either Diovan HCT (valsartan and hydrochlorothiazide 160/12.5 mg once daily) or to valsartan (160 mg once daily) and followed for blood pressure response. Patients were force-titrated at 2-week intervals. Patients on combination therapy were subsequently titrated to 160/25 mg followed by 320/25 mg valsartan/hydrochlorothiazide. Patients on monotherapy were subsequently titrated to 320 mg valsartan followed by a titration to 320 mg valsartan to maintain the blind.

The study randomized 608 patients, including 261 (43%) females, 147 (24%) blacks, and 75 (12%) ≥ 65 years of age. The mean blood pressure at baseline for the total population was 168/112 mmHg. The mean age was 52 years. After 4 weeks of therapy, reductions in systolic and diastolic blood pressure were 9/5 mmHg greater in the group treated with Diovan HCT compared to valsartan. Similar trends were seen when the patients were grouped according to gender, race, or age.

16 HOW SUPPLIED/STORAGE AND HANDLING

Diovan HCT (valsartan and hydrochlorothiazide, USP) is available as non-scored tablets containing valsartan/hydrochlorothiazide 80/12.5 mg, 160/12.5 mg, 160/25 mg, 320/12.5 mg, and 320/25 mg. Strengths are available as follows.

80/12.5 mg Tablet - Light orange, ovaloid, with slightly convex faces debossed CG on 1 side and HGH on the other side.

Bottles of 90 NDC 0078-0314-34

160/12.5 mg Tablet - Dark red, ovaloid, with slightly convex faces debossed CG on 1 side and HHH on the other side.

Bottles of 90 NDC 0078-0315-34

160/25 mg Tablet - Brown orange, ovaloid, with slightly convex faces debossed NVR on 1 side and HXH on the other side.

Bottles of 90 NDC 0078-0383-34

320/12.5 mg Tablet - Pink, ovaloid, with beveled edge, debossed NVR on 1 side and HIL on the other side.

Bottles of 90 NDC 0078-0471-34

320/25 mg Tablet - Yellow, ovaloid, with beveled edge, debossed NVR on 1 side and CTI on the other side.

Bottles of 90 NDC 0078-0472-34

Store at 20°C to 25°C (68°F to 77°F); excursions permitted between 15°C and 30°C (59°F and 86°F) [see USP Controlled Room Temperature].

Protect from moisture.

Dispense in tight container (USP).

17 PATIENT COUNSELING INFORMATION

Information for Patients

Advise the patient to read the FDA-approved patient labeling (Patient Information).

Pregnancy: Advise female patients of childbearing age about the consequences of exposure to Diovan HCT during pregnancy. Discuss treatment options with women planning to become pregnant. Ask patients to report pregnancies to their physicians as soon as possible [see Warnings and Precautions (5.1), Use in Specific Populations (8.1)].

Lactation: Advise women not to breastfeed during treatment with Diovan HCT [see Use in Specific Populations (8.2)].

Symptomatic Hypotension: Advise patients that lightheadedness can occur, especially during the first days of therapy, and that it should be reported to their healthcare provider. Tell patients that if syncope occurs, to discontinue Diovan HCT until the physician has been consulted. Caution all patients that inadequate fluid intake, excessive perspiration, diarrhea, or vomiting can lead to an excessive fall in blood pressure, with the same consequences of lightheadedness and possible syncope [see Warnings and Precautions (5.2)].

Potassium Supplements: Advise patients not to use salt substitutes without consulting their healthcare provider [see Drug Interactions (7)].

Non-melanoma Skin Cancer: Instruct patients taking hydrochlorothiazide to protect skin from the sun and undergo regular skin cancer screening.

T2020-120

FDA-Approved Patient Labeling

PATIENT INFORMATION

DIOVAN HCT® (DYE’-o-van HCT)

(valsartan and hydrochlorothiazide)

Tablets

Read the Patient Information that comes with DIOVAN HCT before you start taking it and each time you get a refill. There may be new information. This leaflet does not take the place of talking with your doctor about your condition and treatment. If you have any questions about DIOVAN HCT, ask your doctor or pharmacist.

What is the most important information I should know about DIOVAN HCT?
DIOVAN HCT can cause harm or death to an unborn baby. Talk to your doctor about other ways to lower your blood pressure if you plan to become pregnant. If you get pregnant while taking DIOVAN HCT, tell your doctor right away.

What is DIOVAN HCT?

DIOVAN HCT contains 2 prescription medicines:

1. valsartan, an angiotensin receptor blocker (ARB)
2. hydrochlorothiazide (HCTZ), a water pill (diuretic)

DIOVAN HCT may be used to lower high blood pressure (hypertension) in adults-

- when 1 medicine to lower your high blood pressure is not enough.
- as the first medicine to lower high blood pressure if your doctor decides you are likely to need more than 1 medicine.

DIOVAN HCT has not been studied in children under 18 years of age.

Who should not take DIOVAN HCT?

Do not take DIOVAN HCT if you:

- are allergic to any of the ingredients in DIOVAN HCT. See the end of this leaflet for a complete list of ingredients in DIOVAN HCT.
- make less urine due to kidney problems.
- are allergic to medicines that contain sulfonamides.

What should I tell my doctor before taking DIOVAN HCT?

Tell your doctor about all your medical conditions, including if you:

- are pregnant or plan to become pregnant. See “What is the most important information I should know about DIOVAN HCT?”
- are breastfeeding. DIOVAN HCT passes into breast milk. It is not known if DIOVAN HCT effects your breastfed baby or milk production. Do not breastfeed while you are taking DIOVAN HCT.
- have liver problems
- have kidney problems
- have or had gallstones
- have Lupus
- have low levels of potassium (with or without symptoms such as muscle weakness, muscle spasms, abnormal heart rhythm) or magnesium in your blood
- have high levels of calcium in your blood (with or without symptoms such as nausea, vomiting, constipation, stomach pain, frequent urination, thirst, muscle weakness and twitching)
- have high levels of uric acid in the blood.
- have ever had a reaction called angioedema, to another blood pressure medication. Angioedema causes swelling of the face, lips, tongue, throat and may cause difficulty breathing

Tell your doctor about all the medicines you take including prescription and nonprescription medicines, vitamins and herbal supplements. Some of your other medicines and DIOVAN HCT could affect each other, causing serious side effects. Especially, tell your doctor if you take:

- other medicines for high blood pressure or a heart problem
- water pills (diuretics)
- potassium supplements. Your doctor may check the amount of potassium in your blood periodically.
- a salt substitute. Your doctor may check the amount of potassium in your blood periodically.
- antidiabetic medicines including insulin
- narcotic pain medicines
- sleeping pills
- lithium, a medicine used in some types of depression (Eskalith®, Lithobid®, Lithium Carbonate, Lithium Citrate)
- aspirin or other medicines called non-steroidal anti-inflammatory drugs (NSAIDs), like ibuprofen or naproxen
- digoxin or other digitalis glycosides (a heart medicine)
- muscle relaxants (medicines used during operations)
- certain cancer medicines, like cyclophosphamide or methotrexate
- certain antibiotics (rifamycin group), a drug used to protect against transplant rejection (cyclosporine) or an antiretroviral drug used to treat HIV/AIDS infection (ritonavir). These drugs may increase the effect of valsartan.

Ask your doctor if you are not sure if you are taking one of these medicines.

Know the medicines you take. Keep a list of your medicines with you to show to your doctor and pharmacist when a new medicine is prescribed. Talk to your doctor or pharmacist before you start taking any new medicine. Your doctor or pharmacist will know what medicines are safe to take together.

How should I take DIOVAN HCT?

- Take DIOVAN HCT exactly as prescribed by your doctor. Your doctor may change your dose if needed.
- Take DIOVAN HCT once each day.
- DIOVAN HCT can be taken with or without food.
- If you miss a dose, take it as soon as you remember. If it is close to your next dose, do not take the missed dose. Just take the next dose at your regular time.
- If you take too much DIOVAN HCT, call your doctor or Poison Control Center, or go to the nearest hospital emergency room.

What should I avoid while taking DIOVAN HCT?

You should not take DIOVAN HCT during pregnancy. See “What is the most important information I should know about DIOVAN HCT?”

What are the possible side effects of DIOVAN HCT?

DIOVAN HCT may cause serious side effects including:

- Harm to an unborn baby causing injury and even death. See “What is the most important information I should know about DIOVAN HCT?”
- Low blood pressure (hypotension). Low blood pressure is most likely to happen if you:
  - take water pills
  - are on a low-salt diet
  - get dialysis treatments
  - have heart problems
  - get sick with vomiting or diarrhea
  - drink alcohol

Lie down if you feel faint or dizzy. Call your doctor right away.

- Allergic reactions. People with and without allergy problems or asthma who take DIOVAN HCT may get allergic reactions.
- Worsening of Lupus. Hydrochlorothiazide, one of the medicines in DIOVAN HCT may cause Lupus to become active or worse.
- Fluid and electrolyte (salt) problems. Tell your doctor about any of the following signs and symptoms of fluid and electrolyte problems:

- dry mouth
- thirst
- lack of energy (lethargic)
- weakness

- drowsiness
- restlessness
- confusion
- seizures
- muscle pain or cramps

- muscle fatigue
- very low urine output
- fast heartbeat
- nausea and vomiting

- Kidney problems. Kidney problems may become worse in people that already have kidney disease. Some people will have changes on blood tests for kidney function and may need a lower dose of DIOVAN HCT. Call your doctor if you get swelling in your feet, ankles, or hands, or unexplained weight gain. If you have heart failure, your doctor should check your kidney function before prescribing DIOVAN HCT.
- Skin rash. Call your doctor right away if you have an unusual skin rash.
- Eye problems. One of the medicines in DIOVAN HCT can cause eye problems that may lead to vision loss. Symptoms of eye problems can happen within hours to weeks of starting DIOVAN HCT. Tell your doctor right away if you have:
  - decrease in vision
  - eye pain

Protect your skin from the sun and undergo regular skin cancer screening, as one of the medicines in DIOVAN HCT may cause non-melanoma skin cancer.

Other side effects were generally mild and brief. They generally have not caused patients to stop taking DIOVAN HCT.

Tell your doctor if you have any side effect that bothers you or that does not go away.

These are not all the possible side effects of DIOVAN HCT. For a complete list, ask your doctor or pharmacist.

Call your doctor for medical advice about side effects. You may report side effects to FDA at 1-800-FDA-1088.

How do I store DIOVAN HCT?

- Store DIOVAN HCT tablets at room temperature between 59°F to 86°F (15°C to 30°C).
- Keep DIOVAN HCT in a closed container in a dry place.

Keep DIOVAN HCT and all medicines out of the reach of children.

General information about DIOVAN HCT

Medicines are sometimes prescribed for conditions that are not mentioned in patient information leaflets. Do not use DIOVAN HCT for a condition for which it was not prescribed. Do not give DIOVAN HCT to other people, even if they have the same symptoms you have. It may harm them.

This leaflet summarizes the most important information about DIOVAN HCT. If you would like more information, talk with your doctor. You can ask your doctor or pharmacist for information about DIOVAN HCT that is written for health professionals. For more information about DIOVAN HCT, go to www.DIOVAN.com or call 1-888-669-6682.

What are the ingredients in DIOVAN HCT?

Active ingredients: Valsartan and hydrochlorothiazide

Inactive ingredients: colloidal silicon dioxide, crospovidone, hydroxypropyl methylcellulose, iron oxides, magnesium stearate, microcrystalline cellulose, polyethylene glycol, talc, and titanium dioxide.

What is high blood pressure (hypertension)?

Blood pressure is the force in your blood vessels when your heart beats and when your heart rests. You have high blood pressure when the force is too much. DIOVAN HCT can help your blood vessels relax and reduce the amount of water in your body so your blood pressure is lower. Medicines that lower blood pressure lower your risk of having a stroke or heart attack.

High blood pressure makes the heart work harder to pump blood throughout the body and causes damage to the blood vessels. If high blood pressure is not treated, it can lead to stroke, heart attack, heart failure, kidney failure, and vision problems.

Eskalith® and Lithobid® are registered trademarks of Noven Pharmaceuticals, Inc.

Distributed by:

Novartis Pharmaceuticals Corporation

East Hanover, New Jersey 07936

© Novartis

T2024-85
Revised: December 2024

PRINCIPAL DISPLAY PANEL

NDC 0078-0314-34

Diovan HCT®

valsartan and hydrochlorothiazide, USP

80 mg/12.5 mg

90 tablets

Rx only

NOVARTIS

PRINCIPAL DISPLAY PANEL

NDC 0078-0315-34

Diovan HCT®

valsartan and hydrochlorothiazide, USP

160 mg/12.5 mg

90 tablets

Rx only

NOVARTIS

PRINCIPAL DISPLAY PANEL

NDC 0078-0383-34

Diovan HCT®

valsartan and hydrochlorothiazide, USP

160 mg/25 mg

90 tablets

Rx only

NOVARTIS

PRINCIPAL DISPLAY PANEL

NDC 0078-0471-34

Diovan HCT®

valsartan and hydrochlorothiazide, USP

320 mg/12.5 mg

90 tablets

Rx only

NOVARTIS

PRINCIPAL DISPLAY PANEL

NDC 0078-0472-34

Diovan HCT®

valsartan and hydrochlorothiazide, USP

320 mg/25 mg

90 tablets

Rx only

NOVARTIS